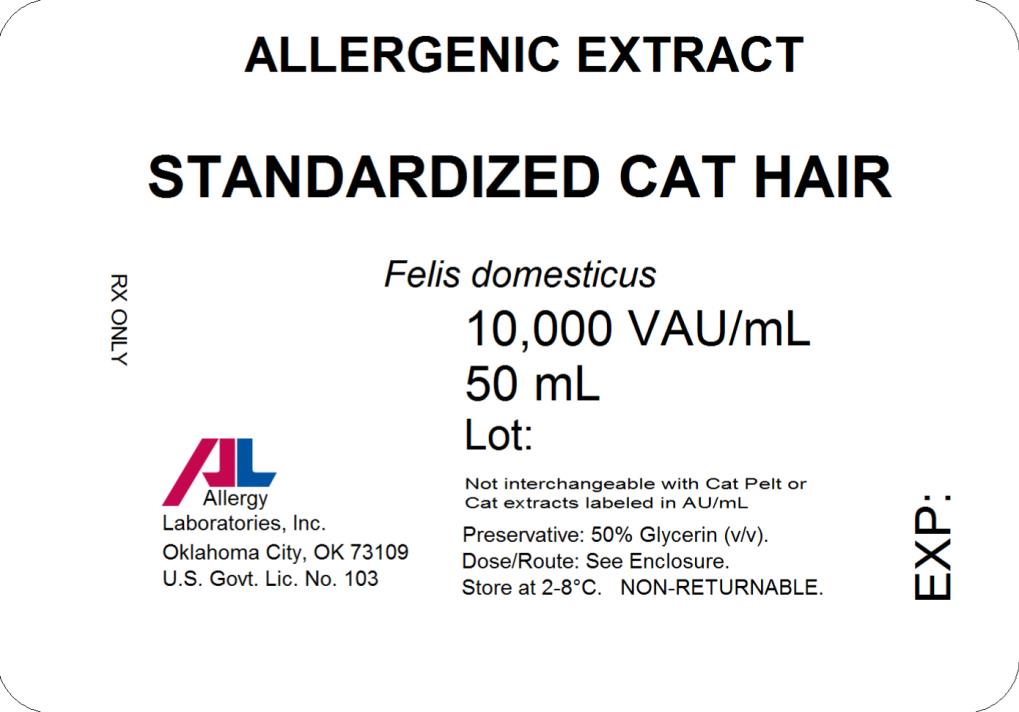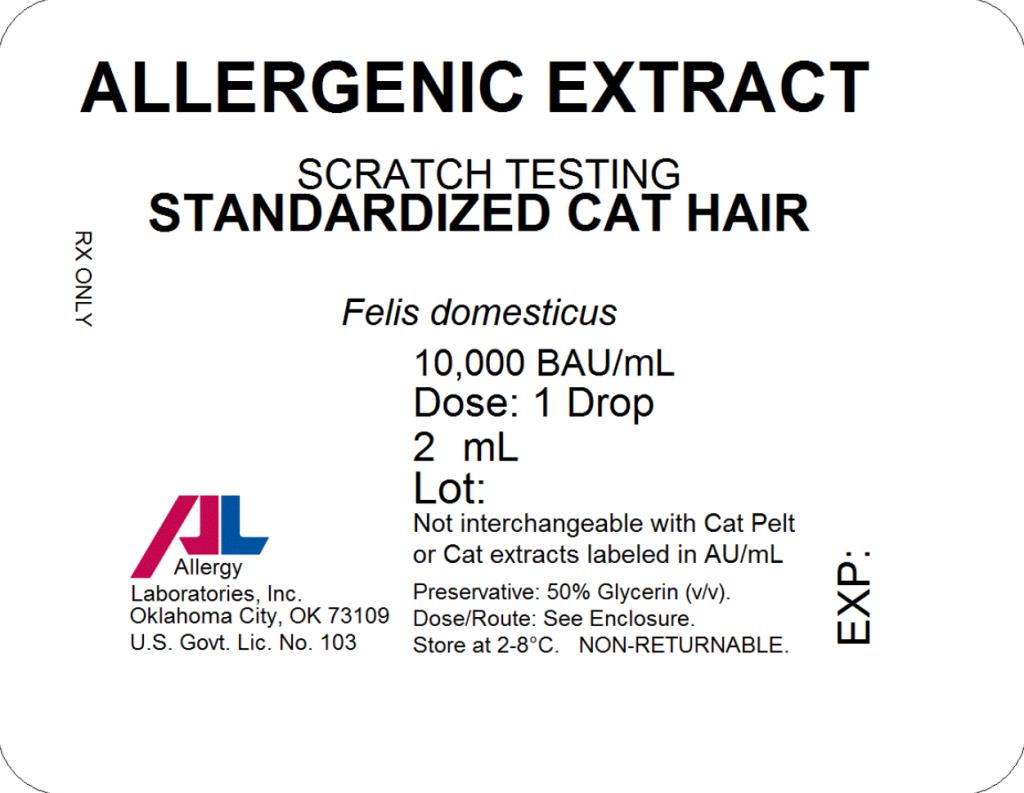 DRUG LABEL: Standardized Cat Hair
NDC: 54575-288 | Form: INJECTION, SOLUTION
Manufacturer: Allergy Laboratories, Inc.
Category: other | Type: STANDARDIZED ALLERGENIC
Date: 20171219

ACTIVE INGREDIENTS: FELIS CATUS HAIR 10000 [BAU]/1 mL
INACTIVE INGREDIENTS: GLYCERIN 0.5 mL/1 mL; SODIUM CHLORIDE 0.00166 g/1 mL; SODIUM BICARBONATE 0.00091 g/1 mL; WATER

Standardized Cat Hair

ALLERGY LABORATORIES, INC.
Oklahoma City, OK 73109

INSTRUCTION AND DOSAGE SCHEDULE FOR STANDARDIZED ALLERGENIC EXTRACTS

CAT HAIR

WARNING

This product is intended for use by physicians who are experienced in the administration of allergenic extracts and the emergency care of anaphylaxis, or for use under the guidance of an allergy specialist.

Extracts standardized using Bioequivalent Allergy Unit (BAU/ml) may be more potent than nonstandardized cat extracts based on the weight to volume, or PNU methods. Allergy Laboratories' standardized cat hair extract is not interchangeable with standardized cat pelt extracts, and also not interchangeable with other standardized cat extracts labelled in Allergy Units (AU/ml). The initial dose must be based on skin testing as described in the dosage and administration section of this insert. Patients being switched from nonstandardized cat extracts to Allergy Laboratories' standardized cat extract should be started as though they were coming under treatment for the first time. Patients should be instructed to recognize adverse reaction symptoms and cautioned to contact the physicians office if reaction symptoms occur. As with all allergenic extracts, severe systemic reactions may occur. In certain individuals these life threatening reactions may be fatal. Patients should be observed for at least 30 minutes following treatment and emergency measures as well as personnel trained in their use should be immediately available in the event of a life threatening reaction.

This product should not be injected intravenously. Subcutaneous injections are recommended.

Patients who are taking non-selective beta blockers may be more reactive to allergens given for testing or treatment and may be unresponsive to the usual doses of epinephrine used to treat allergic reactions.

Refer also to the warnings, precautions, adverse reactions and dosage sections below.

DESCRIPTION

The standardized (BAU/ml) extract in these vials is designed primarily for the physician equipped to prepare dilutions and mixtures as required. The sterile extract is prepared from the extractables of cat hair and cat wash and containes 50% (v/v) glycerine as a preservative. It is intended for subcutaneous injection.

The cat hair extract is assayed for potency using Radial immunodiffusion (1) against a reference extract distributed by the Center for Biologics Evaluation and Research, U.S. Food and Drug Administration. Potency based on Bioequivalent Allergy Units (BAU/ml) is printed on the label. Cat hair extract containing between 10-19.9 Fel d 1 U/ml are labeled 10,000 BAU/ml based on the quantitative skin testing (ID50 EAL Method) (2). Standardized cat hair is compared to an FDA reference cat hair extract by IEF to establish identity.

INACTIVE INGREDIENTS

Glycerinated extracts contain:

glycerine | 50.0 % v/v
sodium chloride | 0.166 % w/v
sodium bicarbonate | 0.091 % w/v

CLINICAL PHARMACOLOGY

The allergic state is initiated by an immune response inducing B cells to produce IgE antibodies to specific allergens. IgE antibodies bind to surface receptors on mast cells and basophils. When antigens gain access to the immune system they react with the bound IgE. The reacting antigen to the surface bound IgE stimulates a number of chemical mediators to be released from the mast cells and basophils. These include histamine, Eosinophil Chemotactic Factor (ECF-A) and leukotrienes. These chemical mediators are pharmacologically active at low concentrations and are partially responsible for the biological manifestation of the allergic response. (3)

The mechanism by which immunotherapy achieves hyposensitization is not completely understood. There is an increase in 'blocking antibody" (IgG) titer and in some patients a decrease in specific IgE, a decrease in histamine release to specific allergen and an increase in suppressor cell population to specific allergen. These changes may occur only after prolonged therapy. (4)

INDICATIONS AND USAGE

Standardized Cat Hair Extracts are indicated for the diagnosis of patients with a history of allergy to cats and for treatment of patients with cat allergy. Diagnosis of allergic disease to cat hair is made through a combined medical history sufficiently complete to identify allergic symptoms to cat hair and identification of cat allergy by diagnostic skin testing.

Hyposensitization therapy is a treatment for patients exhibiting allergic reactions to cat. Immunotherapy is intended for patients whose symptoms cannot be satisfactorily controlled by avoidance of the offending allergen or by the use of symptomatic medications. (5)

CONTRAINDICATIONS

There are no known absolute contraindications to hyposensitization therapy. See precautions section for pregnancy risks.

A patient should not be treated with allergens unless a history of symptoms and a positive skin test reaction have been demonstrated. Allergenic extracts should only be administered to patients that show symptoms of allergy or asthma. The physician must determine if the benefits outweigh the risks in using these products for treating these patients.

Patients who are taking non-selective beta blockers may be more reactive to allergens given for testing or treatment and may be unresponsive to the usual doses of epinephrine used to treat allergic reactions.

WARNINGS

See WARNING at the beginning of the instruction sheet.

Extracts standardized using the Bioequivalent Allergy Unit (BAU/ml) may be more potent than extracts based on weight to volume, or PNU methods. Comparative skin tests can be performed to determine the relative potency before initial use of new extracts. DO NOT GIVE ALLERGY INJECTIONS INTRAVENOUSLY. Subcutaneous injections are recommended. Injections may produce large local reactions that may be painful to the patient. DO NOT GIVE FULL STRENGTH INJECTIONS UNTIL THE COMPARATIVE STRENGTH IS DETERMINED. After inserting the needle, but before injection extract, withdraw the plunger slightly. If blood appears in the syringe, re-insert the needle at another site. Careful selection of dose and injection should prevent most systemic reactions.

PRECAUTIONS

GENERAL

The dosage should be reduced 50-75% from the previous dose when starting a patient on a new lot of standardized cat hair extract from the same manufacturer or from a different manufacturer. When changing from a non-standardized cat hair extract to a standardized cat hair extract, the dose should be based upon comparative skin testing or the patient should be treated as though beginning treatment for the first time.

A separate sterile tuberculin type syringe should be used with each patient to prevent cross contamination of extracts. This will also prevent transmission of disease such as serum hepatitis, AIDS and other infectious diseases. Aseptic technique should always be used when injections of allergic extracts are administered.

CARCINOGENESIS, MUTAGENESIS, IMPAIRMENT OF FERTILITY:

Long term studies with extracts have not been conducted in animals to determine their potential for carcinogenesis, mutagenesis, or impairment of fertility.

PREGNANCY:

Pregnancy Category C. Animal reproduction studies have not been conducted with allergenic extracts. It is also not known whether allergenic extracts can cause fetal harm when administered to a pregnant woman or can affect reproduction capacity. Allergenic extracts should be given to a pregnant woman only if clearly needed.

Controlled studies of hyposensitization with moderate to high doses of allergenic extracts in pregnant women have failed to demonstrate any risk to the mother or fetus. (6)

However, with histamines known ability to contract uterine muscles any reaction which would release significant amounts of histamine such as hyposensitization overdose should be avoided. The physician must weigh the benefits of immunotherapy against the risk of anaphylactic reactions that could result in harm to the mother and/or fetus.

Hyposensitization should be used during pregnancy only if clearly necessary and administered cautiously. If a woman is on maintenance dose the occurrence of pregnancy is not an indication to stop injection therapy.

NURSING MOTHERS:

It is not known if allergenic extracts are excreted in human milk therefore caution should be exercised when extracts are administered in nursing women.

PEDIATRIC USE:

Doses of allergenic extracts for children are generally the same as those for adults. The extracts may cause some pain or discomfort when injected. The maximum tolerated dose may be less than the adult dose due to the smaller size of the child. Therefore, the volume of the dose may need to be adjusted from the adult schedules provided.

DRUG INTERACTIONS:

Patients who are taking non-selective beta blockers may be more reactive to allergens given for testing or treatment and may be unresponsive to the usual doses of epinephrine used to treat allergic reactions. Antihistamines can significantly inhibit the immediate skin test reactions. Patients should be free of such medication for at least 48 hours before testing.

ADVERSE REACTIONS

Local reactions:

Some swelling and redness at the site of injection is not unusual. Mild burning that occurs immediately after the injection is normal; this usually subsides in 10 to 20 seconds. If the swelling and redness persist for a period of 24 hours or longer this should be a sign to proceed with caution in increasing the dosage. With the next injection the dosage should remain the same or be decreased. Large local reactions may indicate that a systemic reaction could occur with the next injection if the dosage was increased. If a patient continues to have reactions at the maintenance dose, the patient is considered to have exceeded the maximum tolerated dosage.

Systemic Reactions:

Systemic reactions occur infrequently but must be looked for in all patients, especially highly sensitive patients. Anaphylactic shock and death are always possible, therefore, physicians must be prepared for the treatment of these reactions. Systemic reactions can also be characterized by one or more of the following symptoms: angioedema, tachycardia, conjunctivitis, cough, fainting, hypotension, pallor, rhinitis, urticaria, and wheezing.

Systemic reaction can be treated by the immediate application of a tourniquet above the site of injection and the administration of 0.3 to 0.5ml of 1:1000 Epinephrine - Hydrochloride subcutaneously or intramuscularly at the site of allergen injection. The dosage may be repeated two times at 15 minute intervals. Loosen the tourniquet at least every 10 minutes.

The pediatric dosage for 1:1000 Epinephrine-Hydrochloride is 0.05 to 0.1ml for infants to 2 years of age; 0.15ml, for children 2 to 6 years; and 0.2ml, for children 6 to 12 years.

Patients should always be observed for at least 30 minutes after any injection. Hypotension can be reversed by using vasopressor agents and volume expanders. Parenteral aminophylline and inhalation bronchodilators may be required for bronchospasm. Oxygen may also be needed. Maintenance of an open airway is critical if upper airway obstruction is present. Adrenal corticosteroids and intravenous antihistamine can be given after adequate epinephrine and circulatory support has been administered. Physicians must be familiar with these systemic reactions and have all the equipment and drugs necessary for proper treatment. (7)

DOSAGE AND ADMINISTRATION

DIAGNOSTIC SKIN TESTING:

Puncture tests performed on 10 highly sensitive patients with 10,000 BAU/ml Cat Hair Extract showed a mean sum of diameter wheal of 17.00mm ± 4.59 and a mean sum of diameter Erythema of 71.60 +14.01.

Intradermal skin test results in highly sensitive patients is shown below, using the same extract as used in the puncture test above.

BAU/ml to elicit 50mm sum of

Diameter of Erythema reaction

Number of Patients

Mean Range

10

0.0128 0.0021-0.1957

These products are used to determine a patient's sensitivity to specific antigens and aid in the diagnosis and treatment of atopic diseases. After a thorough history a decision can be made as to which allergens will be appropriate to use for testing. The recommended procedure is to initially perform puncture tests, then follow with intradermal tests. See recommended dosage below.

SCRATCH OR PUNCTURE TEST:

Concentration BAU/ml

Dosage ml

10,000

0.05 (1 drop)

INTRADERMAL TEST:

A. Patients with a negative scratch or puncture test.

Concentration BAU/ml

Dosage ml

1) 50 BAU/ml

0.02

2) 100 BAU/ml [The negative intradermal control used for the 100 BAU/ml concentration should contain 0.5% (v/v) glycerine.] if 50 BAU/ml is negative

B. Patients tested by intradermal only.

Concentration BAU/ml

Dosage ml

0.5 BAU/ml

0.02

If negative repeat tests with stronger concentrations
until a maximum of 100 BAU/ml is reached.

FREQUENCY OF ADMINISTRATION:

The number of skin tests applied at one time will depend on the particular patient and their allergic history. These tests should be performed and observed in 15 to 20 minutes. Additional tests may be applied in sequence. Perform tests on the anterolateral aspect of the upper arm on an area that permits the effective application of a tourniquet proximal to the site of the test. The skin at the site of injection should be disinfected with rubbing alcohol before testing.

Puncture testing: Apply one drop (0.05ml) of extract to the skin. Pierce the drop of extract and skin using a sterile hypodermic needle or vaccinating needle. Maintain the needle perpendicular to the skin surface and rock the needle back and forth to produce a small hole without bleeding. Do not rotate or gouge the needle. Remove needle from skin and wipe excess extract from skin surface.

Scratch testing: Using a scarifier or needle, make a scratch 1/16 inch long on the epidermis penetrating the outer cornified area but being careful not to draw blood. Apply one drop (0.05ml) of allergen to the scratch.

Intradermal testing: use a separate sterile syringe (tuberculin type equipped with a 27 gauge by 3/8 inch needle with intradermal bevel) for each antigen. The tests are made by injecting 0.02ml of allergen into the epidermis. If the test has been performed properly, the solution should raise a bleb 2 to 3mm in diameter. If the bleb does not appear, the injection was made too deeply.

A negative control consisting of the same solution that the extract was prepared in should be applied to one of the sites in the same manner as the tests being performed. For example, the negative intradermal control should contain 0.5% (v/v) glycerine, if a 100 BAU/ml concentration cat hair is used for intradermal testing. Histamine phosphate should be used as a positive control for evaluation of skin testing. Histamine phosphate is available from other manufacturers. See their directions for use, for recommended dosage and interpretation of results.

A positive reaction usually develops in 15-20 minutes. The positive response is a wheal and flare reaction that is larger than the negative control and judged on the size of the reaction. Scratch or puncture tests may not elicit as large and well defined reaction as the intradermal. (5)

The following system is recommended (8):

 | Reaction | Erythema | Wheal
 | 0 | <5mm | <5mm
 | ± | 5-10mm | 5-10mm
 | 1+ | 11-20mm | 5-10mm
 | 2+ | 21-30mm | 5-10mm
 | 3+ | 31-40mm | 10-15mm or with pseudopods
 | 4+ | >40mm | >15mm or with many pseudopods

IMMUNOTHERAPY:

The following are two methods of injection therapy:

1. Pre-seasonal in which treatment is begun three months before seasonal difficulty begins and brought to maintenance dose by injections four to seven days apart and discontinued after that season ends.
2. Perennial treatment is the recommended mode of therapy in which the patient is, by injection therapy, brought up to tolerated maintenance dose and remains at that dose until amelioration of allergic symptoms occurs. Injections may be given at intervals of 4 to 7 days.

Allergenic extracts must be diluted before use. Normally immunotherapy can be started with a 1 BAU/ml dilution. If a patient appears to be extremely sensitive, dilutions of the antigen can further be made before injections are started. The following are suggested procedures for making a proper dilution series. Recommended diluents contain 0.9% sodium chloride and 0.4% phenol as a preservative.

TEN FOLD DILUTION SERIES:
EXTRACT VOLUME | EXTRACT CONCENTRATION BAU/ml | DILUENT VOLUME | DILUTION CONCENTRATION BAU/ml
1 part | 10,000 + | 9 parts | = 1,000
1 part | 1,000 + | 9 parts | = 100
1 part | 100 + | 9 parts | = 10
1 part | 10 + | 9 parts | = 1
1 part | 1 + | 9 parts | = 0.1
1 part | 0.1 + | 9 parts | = 0.01

Perennial treatment may be started using the following dosage and dilution schedule. THIS SCHEDULE IS ONLY ILLUSTRATIVE AND HAS NOT BEEN SUBJECTED TO ADEQUATE OR WELL-CONTROLLED TRIALS TO DETERMINE EITHER ITS SAFETY OR EFFICACY.

DOSE # | DOSE VOLUME | CONCENTRATION
1 | 0.05 | 1 BAU/ml
2 | 0.10
3 | 0.20
4 | 0.30
5 | 0.40
6 | 0.50
7 | 0.05 | 10 BAU/ml
8 | 0.10
9 | 0.20
10 | 0.30
11 | 0.40
12 | 0.50
13 | 0.05 | 100 BAU/ml
14 | 0.10
15 | 0.20
16 | 0.30
17 | 0.40
18 | 0.50
19 | 0.05 | 1,000 BAU/ml
20 | 0.10
21 | 0.20
22 | 0.30
23 | 0.40
24 | 0.50
25 | 0.05 | 10,000 BAU/ml
26 | 0.10
27 | 0.20
28 | 0.30
29 | 0.40
30 | 0.50

Gradually increase the dose as outlined in the schedule. If you give a dose that causes a mild local reaction manifested by warmth or redness, repeat the same dose. If the reaction is severe or systemic (manifested as hives, asthma, or hay fever), drop back a dose in schedule and build again. If a severe local reaction or a systemic reaction is again encountered, this should be considered more than the maximum tolerance for this patient. The maintenance dose is the largest dose that relieves symptoms without producing local reactions. The size and interval of doses will vary and can be adjusted as necessary. The normal interval between doses is 4 to 7 days.

HOW SUPPLIED

Bulk extract (stock concentrate) in 50% (v/v) glycerine containing 10,000 BAU/ml is supplied in 10ml, 30ml, and 50ml vials. Scratch testing in 50% (v/v) glycerine containing 10,000 BAU/ml is supplied in 2ml dropper vials. Intradermal testing (aqueous) containing 100 BAU/ml is supplied in 5ml vials.

STORAGE

These extracts should be stored at 2 to 8 degrees Celsius. Excessive heating (above room temperature) and repeated freeze-thawing should be avoided. The dating period (expiration date) is shown on the vial label. Once extracts are diluted the shelf life decreases. Extracts should be re-ordered when out of date. Please allow a minimum of three (3) weeks for delivery due to the holding period for sterility testing.

Revised 09/23/92

L-049-00

REFERENCES

1. Anderson, M.C., Baer, H.: Methodology for Assay of Cat Allergen 1 May 1986, In Methods of the Laboratory of Allergenic Products, Division of Bacterial Products, Food and Drug Administration.
2. Turkeltaub, P.C., Rastogi, S.C., Baer, H.: Assignment of Allergy Units to Reference Preparations using the ID50 EAL Method, May 1986, In Methods of the Laboratory of Allergenic Products, Division of Bacterial Products, Food and Drug Administration.
3. Wasserman, S.I.: Biochemical mediators of allergic reactions. In Patterson, R. (ed): Allergic diseases: diagnosis and management, p. 86. Philadelphia, J.B. Lippincott Co. 1985.
4. Grammer, L.C.: Principle of immunologic management of allergic diseases due to extrinsic antigens. In Patterson, R. (ed): Allergic diseases: diagnosis and management, p. 358. Philadelphia, J.B. Lippincott Co. 1985.
5. Booth, B.H.: Diagnosis of Immediate Hypersensitivity. In Patterson, R. (ed): Allergic diseases: diagnosis and management, p. 102. Philadelphia, J.B. Lippincott Co. 1985.
6. Metzger, W.J., et al.: The safety of immunotherapy during pregnancy. J. Allergy Clin. Immunol., 64 (4): 268-272, 1978.
7. Patterson, R. et al.: Immunotherapy. In Middleton, E. Jr., Reed, C.E. and Ellis, E.F. (ed): Allergy; Principles and Practice, (Vol. 2) p. 1119. St. Louis, The C.V. Mosby Co. 1983.
8. Norman, P.S.: In vivo methods of study of allergy: Skin and Mucosal tests, techniques and interpretation. In Middleton, E. Jr., Reed, C.E. and Ellis, E.F. (ed): Allergy Principles and Practice, (Vol 1), p. 258. St. Louis, The C.V. Mosby Co. 1978.

ALLERGY LABORATORIES, INC.
Oklahoma City, OK 73109
U.S. License #103
(405) 235-1451 • 800 654-3971

PRINCIPAL DISPLAY PANEL

ALLERGENIC EXTRACT
STANDARDIZED CAT HAIR
Felis domesticus
10,000 BAU/mL
50 mL
RX ONLY

PRINCIPAL DISPLAY PANEL

ALLERGENIC EXTRACT
SCRATCH TESTING
STANDARIZED CAT HAIR
Felis domesticus
10,000 BAU/mL
Dose: 1 Drop
2 mL
RX ONLY